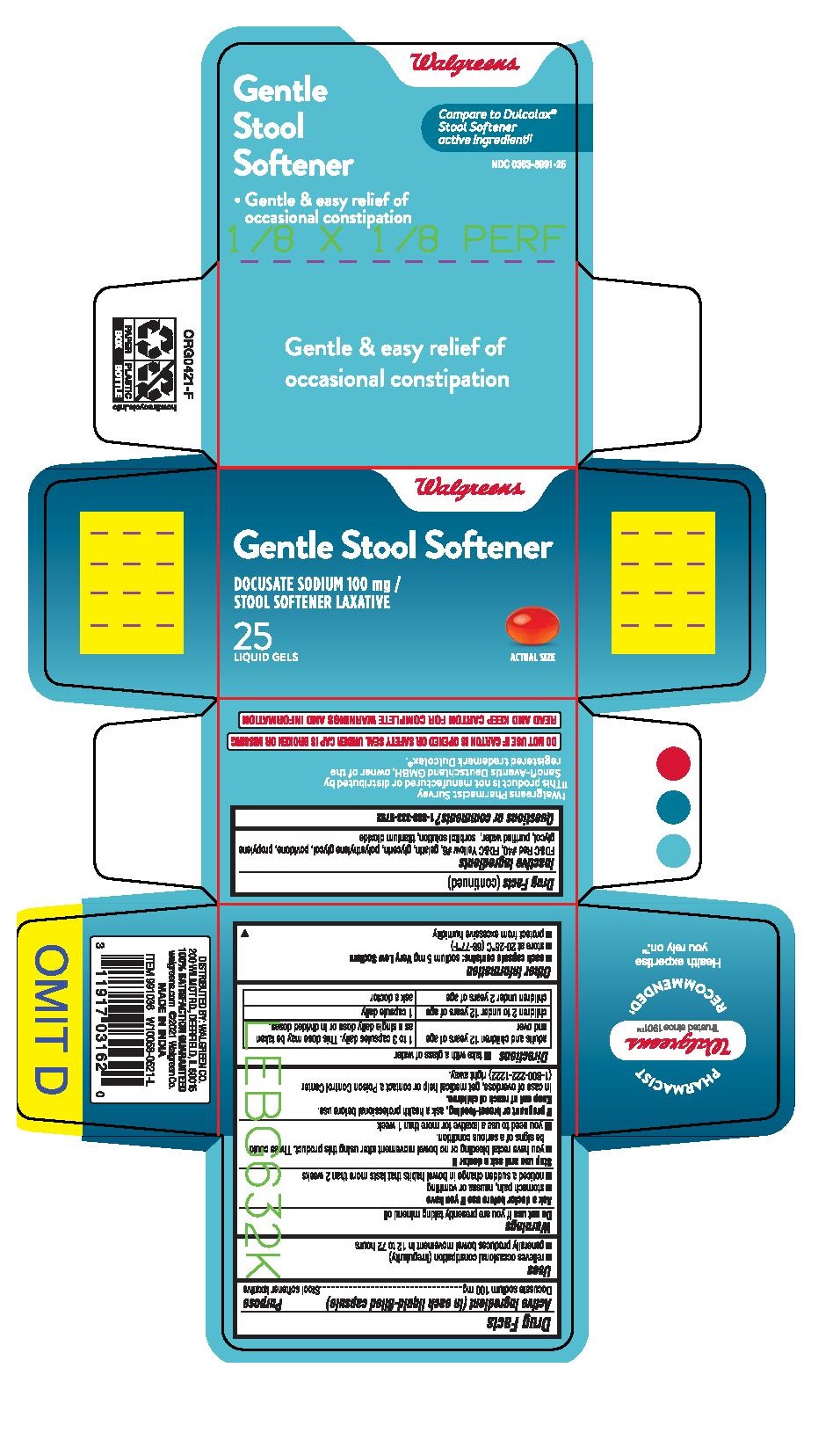 DRUG LABEL: DOCUSATE SODIUM
NDC: 0363-8991 | Form: CAPSULE, LIQUID FILLED
Manufacturer: WALGREEN COMPANY
Category: otc | Type: HUMAN OTC DRUG LABEL
Date: 20260119

ACTIVE INGREDIENTS: DOCUSATE SODIUM 100 mg/1 1
INACTIVE INGREDIENTS: POLYETHYLENE GLYCOL 400; PROPYLENE GLYCOL; WATER; GELATIN; GLYCERIN; SORBITOL; FD&C RED NO. 40; FD&C YELLOW NO. 6; TITANIUM DIOXIDE; POVIDONE K30

Walgreens Gentle Stool Softener

Drug Facts

Active ingredient (in each liquid-filled capsule)

Docusate Sodium 100 mg

Purpose

Stool Softner laxative

Uses

- relieves of occasional constipation (irregularity)
- this product generally produces a bowel movement within 12 to 72 hours

Warnings

Ask a doctor before use if you have

- stomach pain, nausea or vomittiong
- a sudden change in bowel habits that lasts more than 2 weeks

Do not use if you are presently taking mineral oil, unless told to do so by a doctor

Stop use and ask a doctor if you

- you have rectal bleeding ot no bowel movement after using this product. These could be signs of a serious condition.
- yo need to use laxative for more than 1 week

PREGNANCY OR BREAST FEEDING

If pregnant or breast-feeding,ask a health professional before use

Keep out of reach of children. In case of overdose, get medical help or contact a Poison Control Center right away.1(800)222-1222

Directions

take with a glass of water

take by mouth. Doses may be taken as a single daily dose or in divided doses.

Adults and children 12 years and over | take 1 to 3 capsules daily.
Children 2 to under 12 years of age | 1 capsule daily.
Children under 2 years of age | Ask a doctor

Other information

- Store at room temperature 20-25°C (68-77°F)
- protect from excessive humidity
- do not use this product of the safety seal under the cap is torn or missing

Inactive ingredients

FD&C Red#40, FD&C Yellow#6, gelatin,glycerin, polyethylene glycol 400, propylene glycol, povidone, purified water, sorbitol solution, titanium dioxide.

Questions or comments?

1-888-333-9792

PRINCIPAL DISPLAY PANEL

Compare to Dulcolax ® Stool Softener active ingredient *

GENTLE STOOL SOFTENER

DOCUSATE SODIUM 100 mg / STOOL SOFTENER LAXATIVE

25 LIQUID GELS